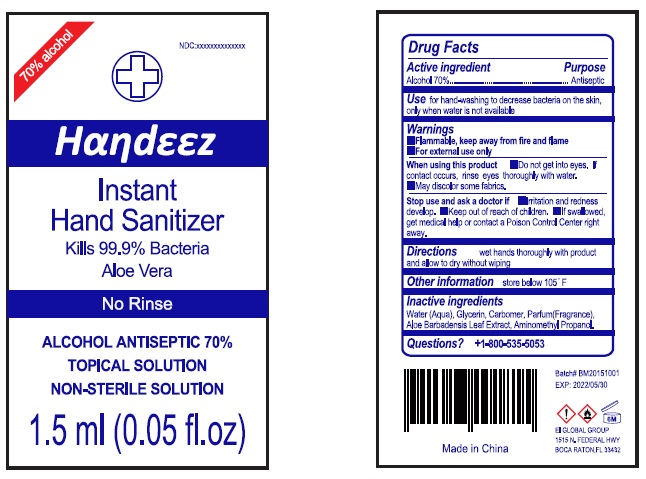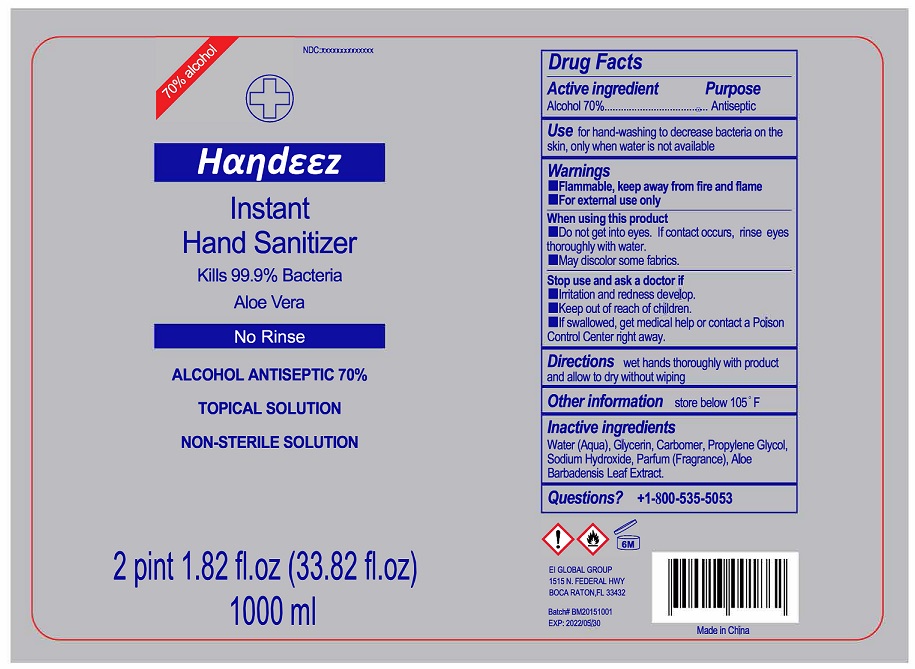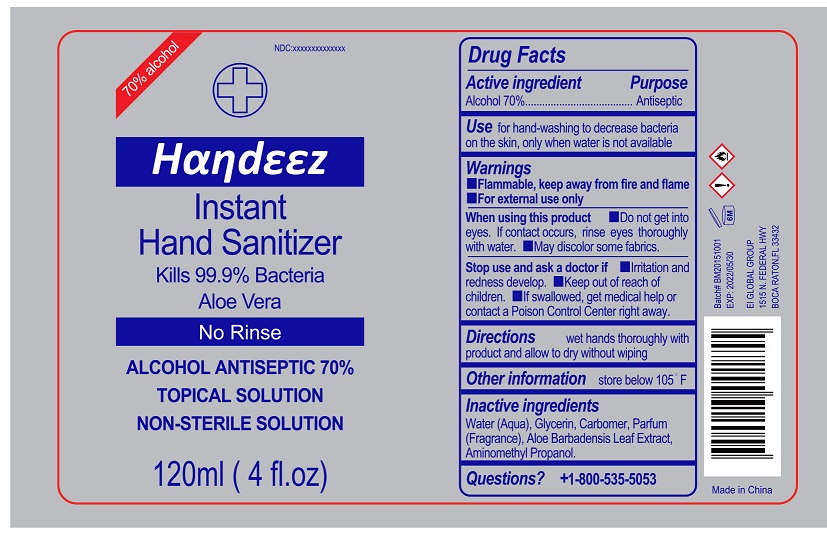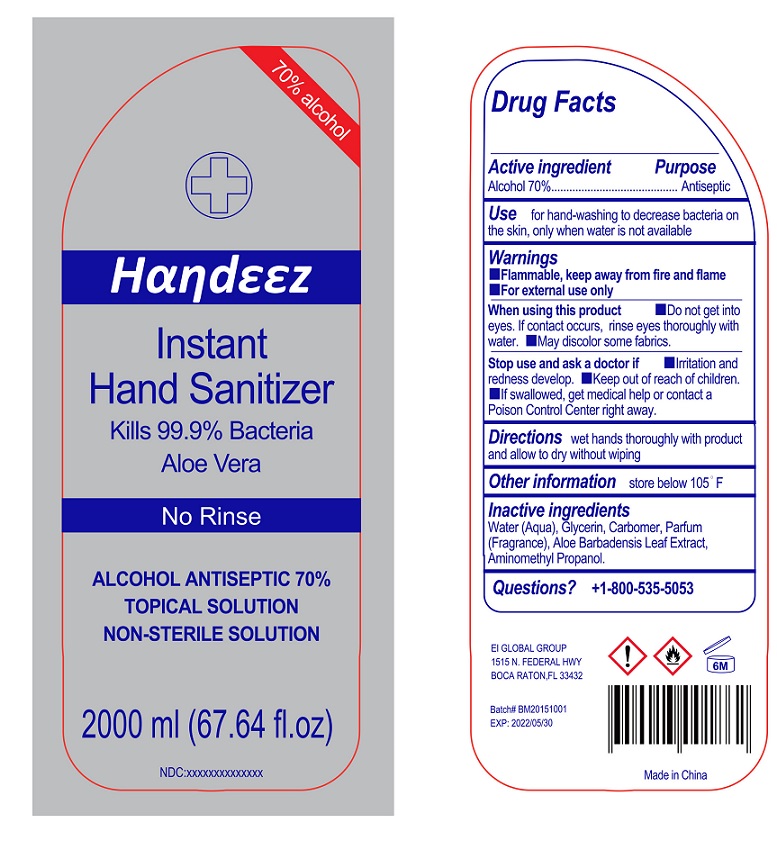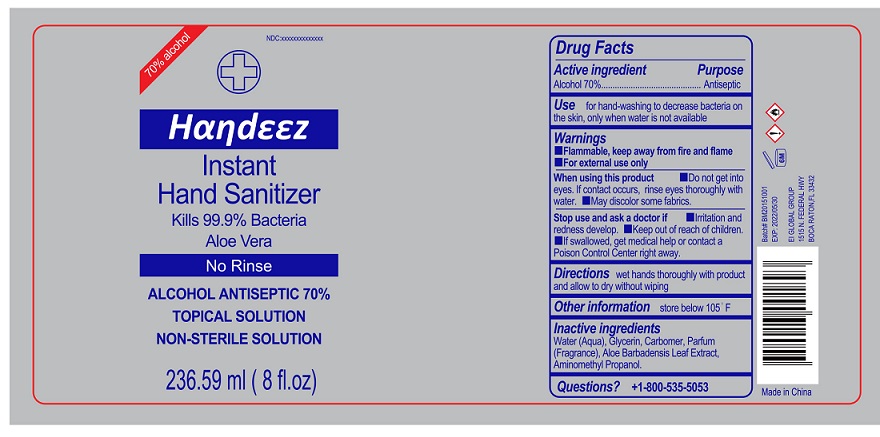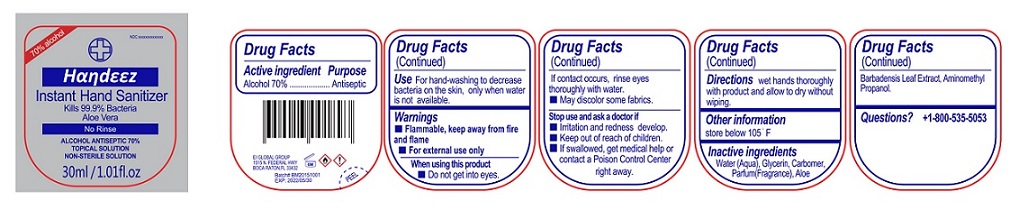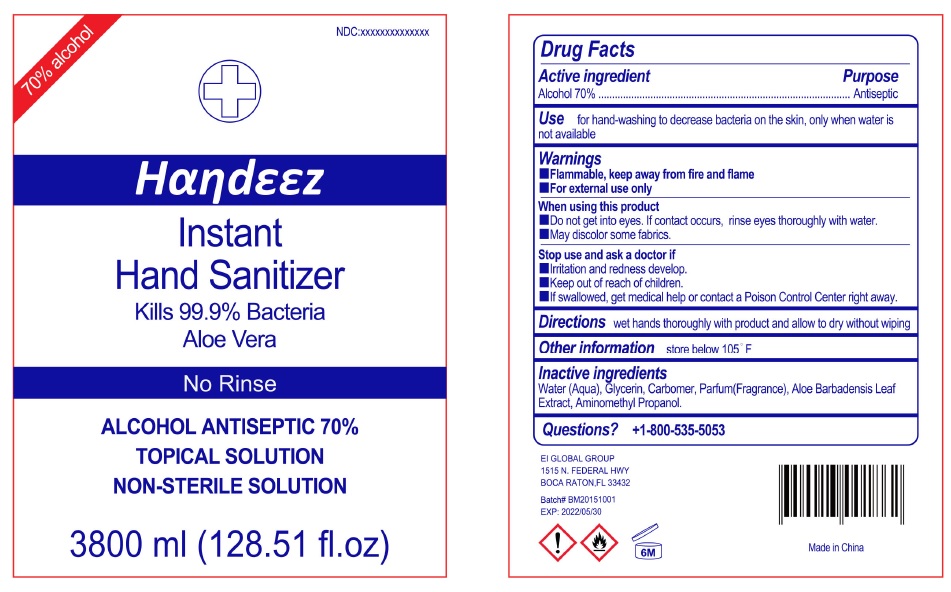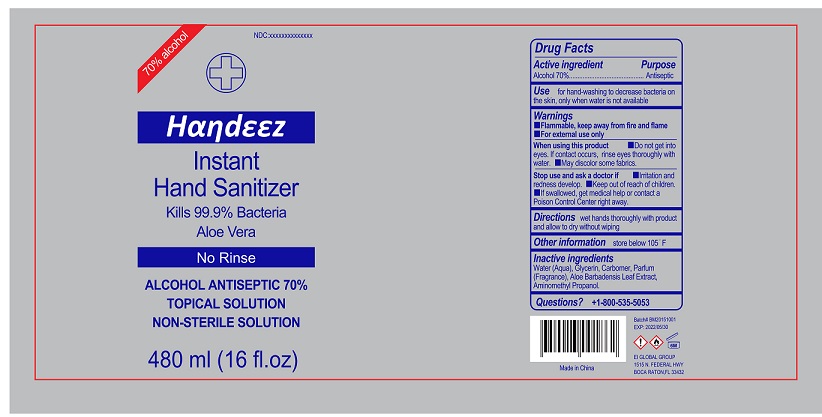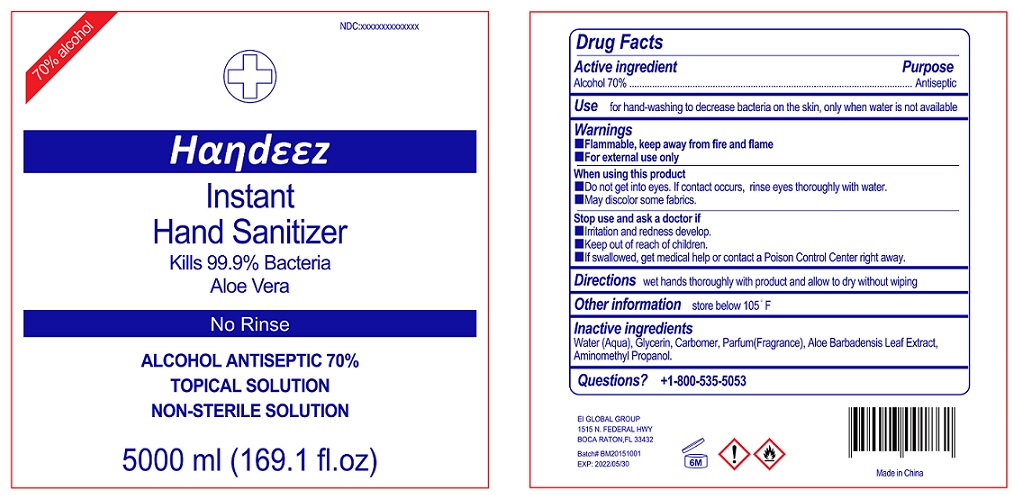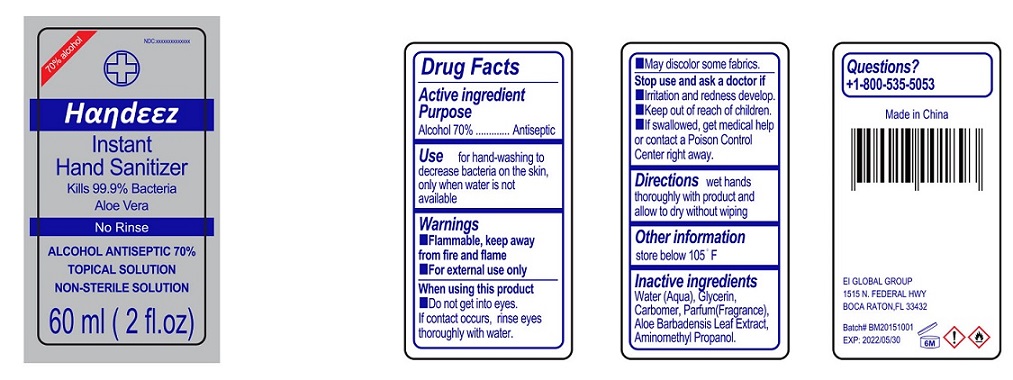 DRUG LABEL: Handeez Instant Hand Sanitizer
NDC: 71203-001 | Form: GEL
Manufacturer: EI GLOBAL GROUP LLC
Category: otc | Type: HUMAN OTC DRUG LABEL
Date: 20200613

ACTIVE INGREDIENTS: ALCOHOL 70 1/100 mL
INACTIVE INGREDIENTS: WATER; GLYCERIN; AMINOMETHYLPROPANOL; ALOE VERA LEAF; CARBOMER 940

Handeez Instant Hand Sanitizer

Active Ingredients

Alcohol 70%.

Purpose

Antiseptic

Warnings

Flammable, keep away from fire and flame.

For external use only.

When using this product

- Do not get into eyes.
- If contact occurs, rinse eyes thoroughly with water.
- May discolor some fabrics.

Stop use and ask a doctor.

- if Irritation and redness develop.

Uses

Instant Hand Sanitizer Topical 70% Alcohol Solution.

Directions

wet hands thoroughly with product and allow to dry without wiping.

Keep out of reach of children.

lf swallowed, get medical help or contact a Poison Control Center right away.

Other Information

store below 105°F.

Inactive Ingredients

Water (Aqua), Glycerin, Carbomer, Perfume (Fragrance), Aloe Barbadensis Leaf Extract, Aminomethyl Propanol.